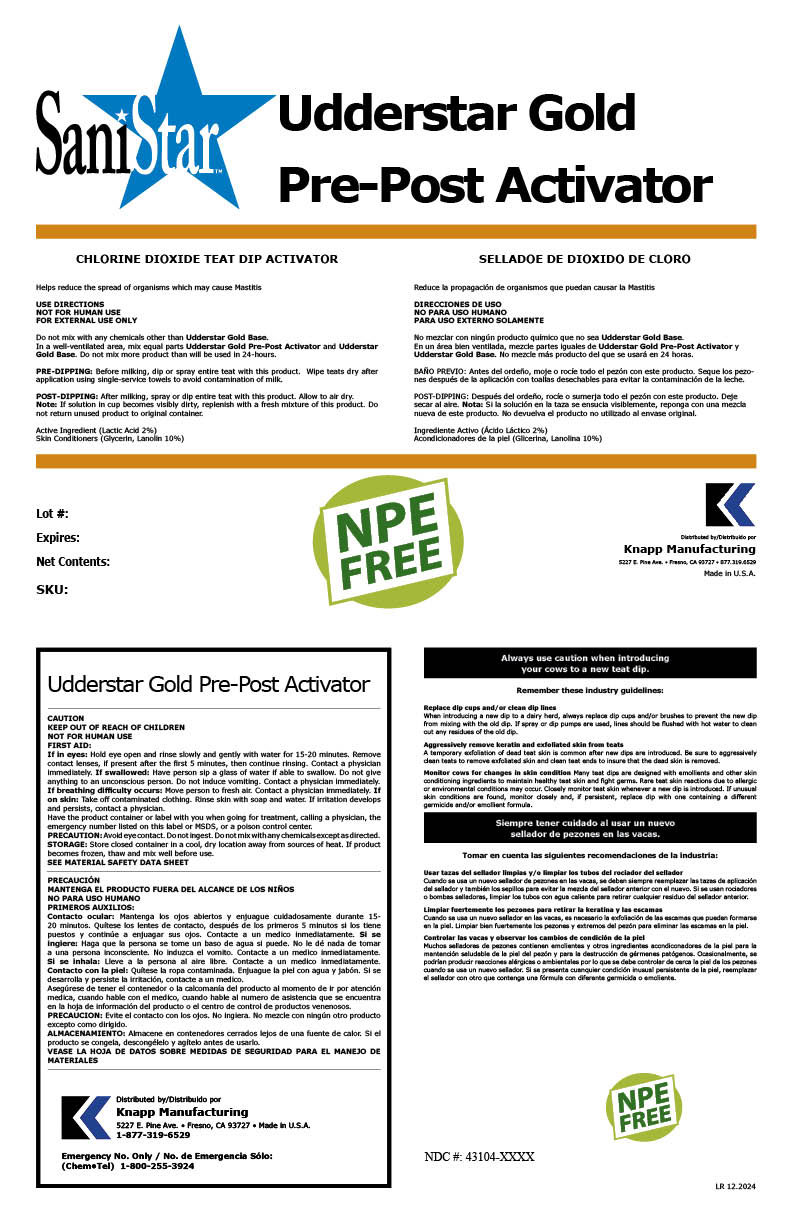 DRUG LABEL: Udderstar Gold Pre-Post Activator
NDC: 43104-2026 | Form: LIQUID
Manufacturer: Knapp Manufacturing, Inc.
Category: animal | Type: OTC ANIMAL DRUG LABEL
Date: 20241219

ACTIVE INGREDIENTS: LACTIC ACID 2.2 kg/1 kg

Udderstar Gold Pre-Post Activator

Claim of effectiveness.

Helps reduce the spread of organisms
which may cause Mastitis

Use Directions

NOT FOR HUMAN USE
FOR EXTERNAL USE ONLY
Do not mix with any chemicals other than Udderstar Gold Base.

In a well-ventilated area, mix equal parts Udderstar Gold Base and Uddestar Gold Pre-Post Activator.

Do not mix more product than will be used in 24 hours.

PRE-DIPPING: Before milking, dip or spray entire teat with this product. Wipe teats dry after
application using single-service towels to avoid contamination of milk.
POST-DIPPING: After milking, spray or dip entire teat with this product. Allow to air dry.
Note: If solution in cup becomes visibly dirty, replenish with a fresh mixture of this product. Do
not return unused product to original container.

First Aid

If in eyes: Hold eye open and rinse slowly and gently with water for 15-20 minutes. Remove
contact lenses, if present after the first 5 minutes, then continue rinsing. Contact a physician
immediately. If swallowed: Have person sip a glass of water if able to swallow. Do not give
anything to an unconscious person. Do not induce vomiting. Contact a physician immediately.
If breathing difficulty occurs: Move person to fresh air. Contact a physician immediately. If
on skin: Take off contaminated clothing. Rinse skin with soap and water. If irritation develops
and persists, contact a physician.
Have the product container or label with you when going for treatment, calling a physician, the
emergency number listed on this label or MSDS, or a poison control center.

Precautions & Hazards

Avoid eye contact. Do not ingest. Do not mix with any chemicals except as directed.

Storage

Store closed container in a cool, dry location away from sources of heat. If product
becomes frozen, thaw and mix well before use.